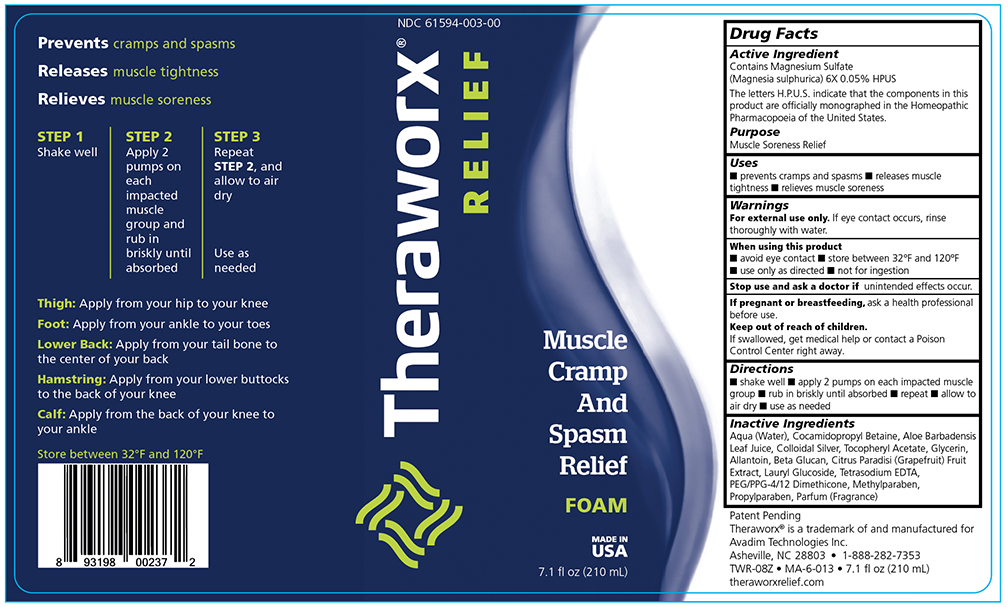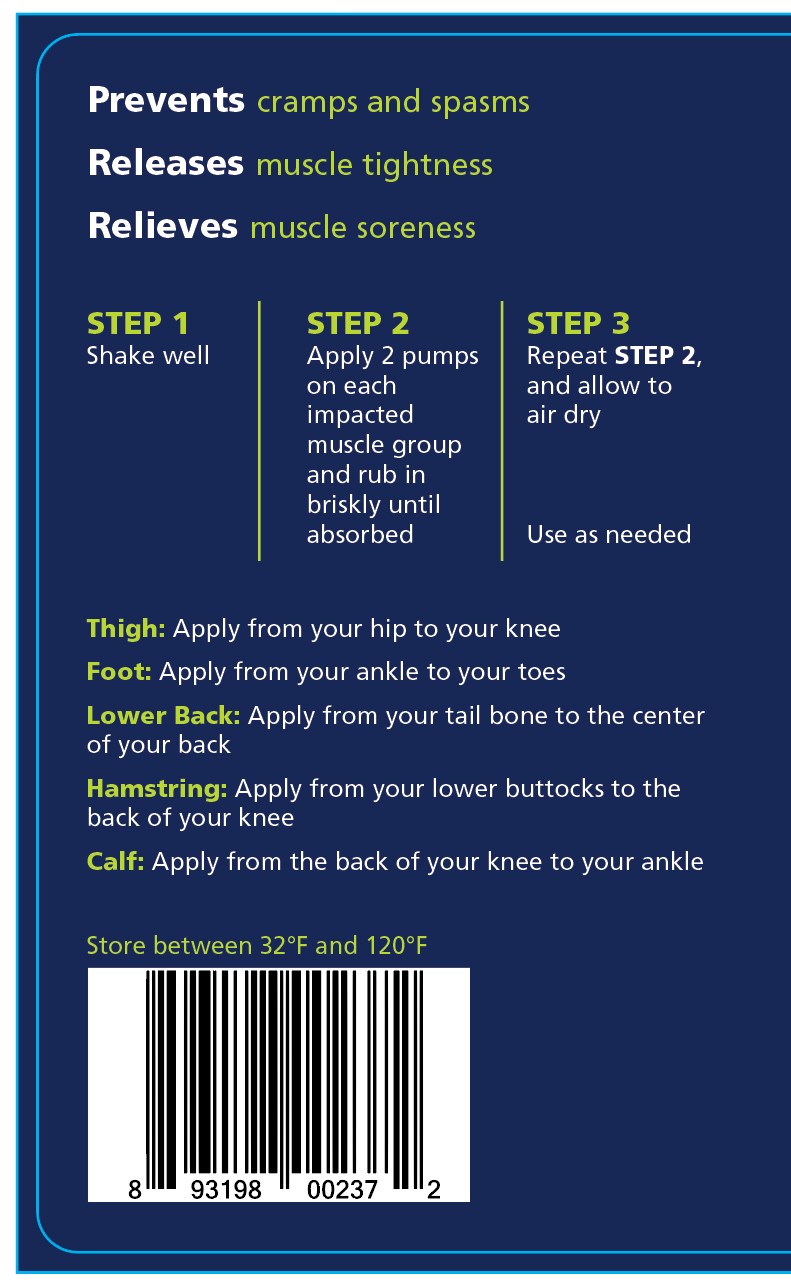 DRUG LABEL: Theraworx Relief Muscle Cramp and Spasm Relief
NDC: 71064-0003 | Form: AEROSOL, FOAM
Manufacturer: Relion Manufacturing
Category: homeopathic | Type: HUMAN PRESCRIPTION DRUG LABEL
Date: 20201207

ACTIVE INGREDIENTS: MAGNESIUM SULFATE HEPTAHYDRATE 6 [hp_X]/1 mL
INACTIVE INGREDIENTS: METHYLPARABEN

Theraworx Relief Muscle Cramp and Spasm Relief